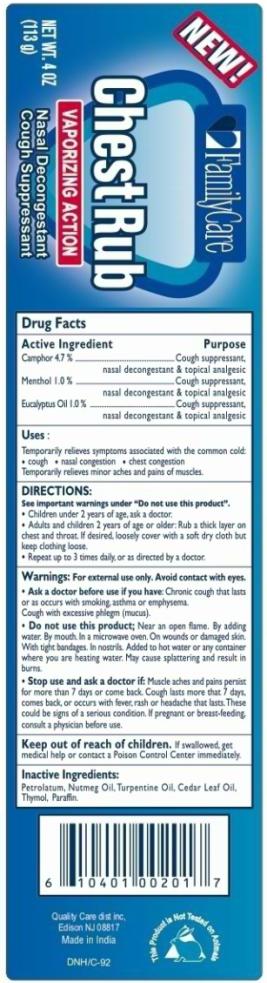 DRUG LABEL: Vaporizing Chest Rub
NDC: 52271-158 | Form: GEL
Manufacturer: Quality Care Distributors LLC
Category: otc | Type: HUMAN OTC DRUG LABEL
Date: 20100725

ACTIVE INGREDIENTS: CAMPHOR (SYNTHETIC) 5.31 g/113 g; EUCALYPTUS OIL 1.13 g/113 g; MENTHOL 1.13 g/113 g
INACTIVE INGREDIENTS: PETROLATUM; PARAFFIN; NUTMEG OIL; TURPENTINE; THYMOL; CEDAR LEAF OIL

Vaporizing Chest Rub

Drug Facts

Active Ingredients

Camphor 4.7%

Menthol 1.0%

Eucalyptus Oil 1.0%

Purpose

Cough suppressant, nasal decongestant & topical analgesic

Use:

Temporarily relives symptoms associated with the common cold:

- cough
- nasal congestion
- chest congestion

Temporarily relieves minor aches and pains of muscles.

Directions:

See important warning under

“Do not use this product”

- Children under 2 years of age, ask a doctor.
- Adults and children 2 years of age or older: Rub a thick layer on chest and throat. If desired, loosely cover with a soft dry cloth but keep clothing loose.
- Repeat up to 3 times daily, or as directed by a doctor.

Warnings:

For external use only: Avoid contact with eyes

Ask a doctor before use if you have:

Chronic cough that lasts or as occurs with smoking, asthma or emphysema. Cough with excessive phlegm (mucus).

Do not use this product;

Near an open flame. By adding water. By mouth. In a microwave oven. On wounds or damaged skin. With tight bandages. In nostrils. Added to hot water or any container where you are heating water. May cause splattering and result in burns.

Stop use and ask a doctor if:

Muscles aches and pains persist for more than 7 days or come back. Cough lasts more that 7 days comes back, or occurs with fever, rash, or headache that lasts. These could be signs of a serious condition. If pregnant or breast-feeding, consult a physician before use

Keep out of reach of children.

If swallowed, get medical helps or contact a Poison Control Center immediately

Inactive Ingredients:

Petrolatum, Nutmeg Oil, Turpentine Oil, Cedar Leaf Oil, Thymol, Paraffin.

Principal Display Panel

NEW!
FamilyCare
Chest Rub
VAPORIZING ACTION
Nasal Decongestant
Cough Suppressant
NET WT. 4 OZ
(113g)